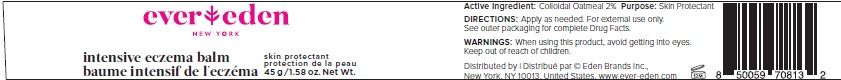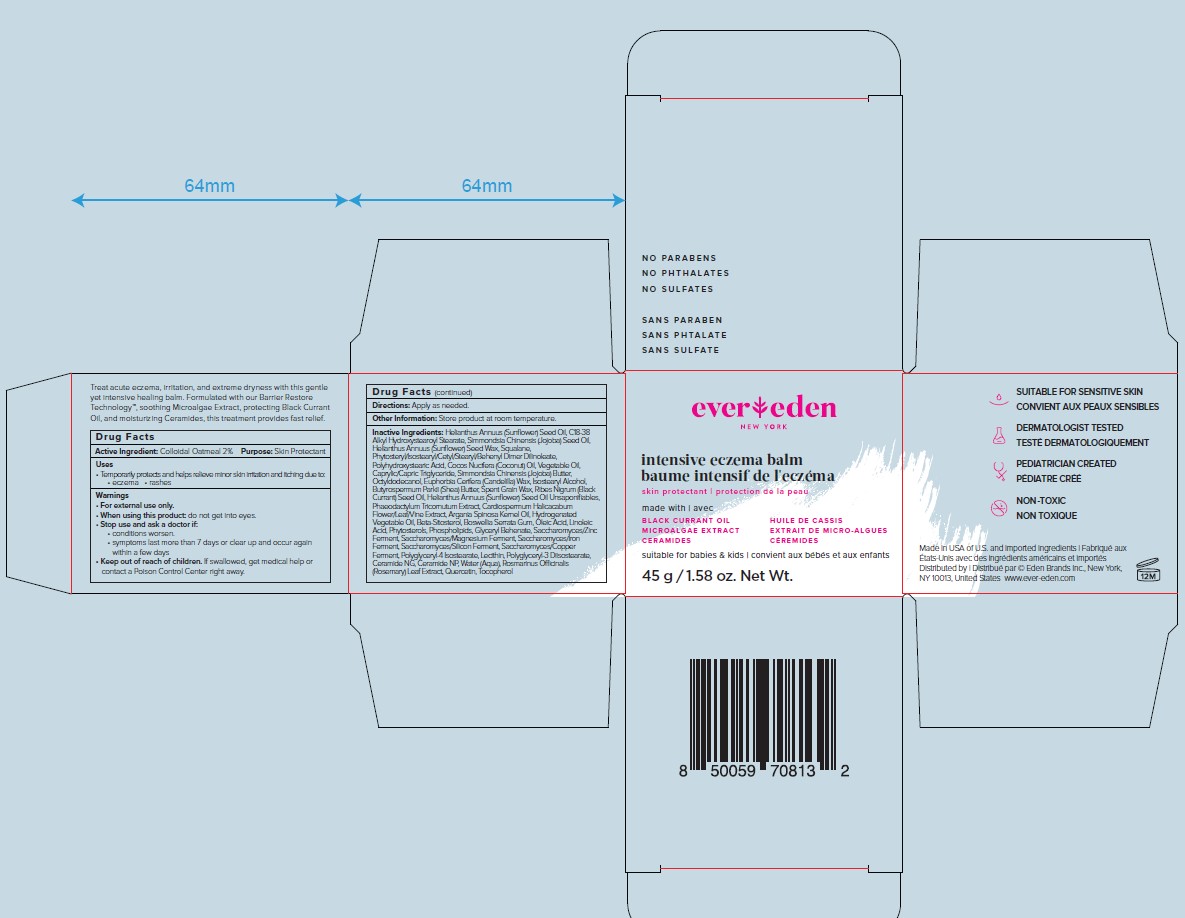 DRUG LABEL: Evereden Intensive Eczema Balm
NDC: 72113-109 | Form: OINTMENT
Manufacturer: Eden Brands Inc.
Category: otc | Type: HUMAN OTC DRUG LABEL
Date: 20240916

ACTIVE INGREDIENTS: OATMEAL 2 g/100 g
INACTIVE INGREDIENTS: POLYHYDROXYSTEARIC ACID (2300 MW); CANDELILLA WAX; RIBES NIGRUM SEED OIL; LECITHIN, SUNFLOWER; PHAEODACTYLUM TRICORNUTUM; HELIANTHUS ANNUUS SEED WAX; OCTYLDODECANOL; ISOSTEARYL ALCOHOL; SUNFLOWER OIL UNSAPONIFIABLES; POLYGLYCERYL-4 ISOSTEARATE; WATER; C18-38 ALKYL HYDROXYSTEAROYL STEARATE; .BETA.-SITOSTEROL; INDIAN FRANKINCENSE; TOCOPHEROL; CERAMIDE NP; ROSEMARY; SUNFLOWER OIL; JOJOBA OIL; SQUALANE; CARDIOSPERMUM HALICACABUM LEAF; CORN OIL; MEDIUM-CHAIN TRIGLYCERIDES; JOJOBA BUTTER; SHEA BUTTER; ARGAN OIL; OLEIC ACID; LINOLEIC ACID; OMEGA-3 FATTY ACIDS; GLYCERYL DIBEHENATE; POLYGLYCERYL-3 DIISOSTEARATE; CERAMIDE NG; QUERCETIN; PHYTOSTERYL/ISOSTEARYL/CETYL/STEARYL/BEHENYL DIMER DILINOLEATE; COCONUT OIL

Intensive Eczema Balm

ACTIVE INGREDIENT

Colloidal Oatmeal 2%

PURPOSE

Skin Protectant

USES:

Temporarily protects and helps relieve minor skin irritation and itching due to:

- Eczema
- Rashes

WARNINGS

For external use only

When using this product: Do not get into eyes

Stop use and ask a doctor if:

- Conditions worsen
- Symptoms last more than 7 days or clear up and occur again within a few days

Keep out of reach of children. If swallowed, get medical help or contact a Poison Control Center right away.

DOSAGE AND ADMINISTRATION

Directions: Use as needed.

Other Information: Store product at room temperature

INACTIVE INGREDIENT

Helianthus Annuus (Sunflower) Seed Oil, C18-38 Alkyl Hydroxystearoyl Stearate, Simmondsia Chinensis (Jojoba) Seed Oil, Helianthus Annuus (Sunflower) Seed Wax, Squalane, Phytosteryl/Isostearyl/Cetyl/Stearyl/Behenyl Dimer Dilinoleate, Polyhydroxystearic Acid, Cocos Nucifera (Coconut) Oil, Vegetable Oil, Caprylic/Capric Triglyceride, Simmondsia Chinensis (Jojoba) Butter, Octyldodecanol, Euphorbia Cerifera (Candelilla) Wax, Isostearyl Alcohol, Butyrospermum Parkii (Shea) Butter, Spent Grain Wax, Ribes Nigrum (Black Currant) Seed Oil, Helianthus Annuus (Sunflower) Seed Oil Unsaponifiables, Phaeodactylum Tricornutum Extract, Cardiospermum Halicacabum Flower/Leaf/Vine Extract, Argania Spinosa Kernel Oil, Hydrogenated Vegetable Oil, Beta-Sitosterol, Boswellia Serrata Gum, Oleic Acid, Linoleic Acid, Phytosterols, Phospholipids, Glyceryl Behenate, Saccharomyces/Zinc Ferment, Saccharomyces/Magnesium Ferment, Saccharomyces/Iron Ferment, Saccharomyces/Silicon Ferment, Saccharomyces/Copper Ferment, Polyglyceryl-4 Isostearate, Lecithin, Polyglyceryl-3 Diisostearate, Ceramide NG, Ceramide NP, Water (Aqua), Rosmarinus Officinalis (Rosemary) Leaf Extract, Quercetin, Tocopherol